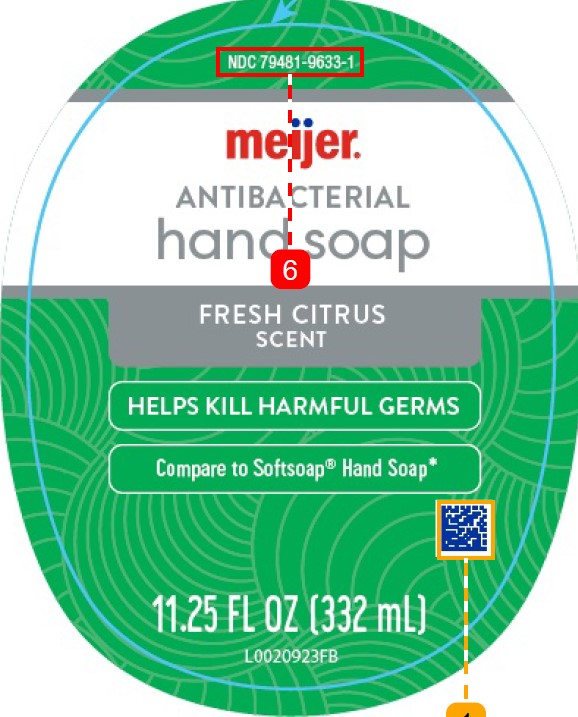 DRUG LABEL: Moisturizing Antibacterial
NDC: 79481-9633 | Form: SOAP
Manufacturer: Meijer, Inc.
Category: otc | Type: HUMAN OTC DRUG LABEL
Date: 20260219

ACTIVE INGREDIENTS: BENZALKONIUM CHLORIDE 1.3 mg/1 mL
INACTIVE INGREDIENTS: WATER; LAURAMINE OXIDE; COCAMIDOPROPYL BETAINE; LAURAMIDOPROPYLAMINE OXIDE; SODIUM CHLORIDE; MYRISTAMIDOPROPYLAMINE OXIDE; GLYCERIN; DISTEARETH-75 ISOPHORONE DIISOCYANATE; PEG-150 DISTEARATE; CITRIC ACID MONOHYDRATE; EDETATE SODIUM; SULISOBENZONE; SODIUM BENZOATE; ORANGE OIL; GREEN TEA LEAF; GINGER OIL; FD&C BLUE NO. 1; FD&C YELLOW NO. 5

Meijer 633.002/633AD
Antibacterial Hand Soap with Moisturizers – Fresh Citrus

Inactive ingredient

Benzalkonium chloride 0.13%

Purpose

Antibacterial

Use

for handwashing to decrease bacteria on the skin

Warnings

For external use only: hands only

When using this product

- avoid contact with eyes. If contact occurs, rinse eyes thoroughly with water

Stop use and ask a doctor if

- irritation and redness develop
- condition persists for more than 72 hours

Keep out of reach of children

If swallowed, get medical help or contact a Poison Control Center right away.

Directions

- wet hands
- apply palmful to hands
- scrub thoroughly
- rinse thoroughly

Inactive ingredients

water, lauramine oxide, cocamidopropyl betaine, lauramidopropylamine oxide, sodium chloride, myristamidopropylamine oxide, glycerin, fragrance, disteareth-75 IPDI, PEG-150 distearate, citric acid, tetrasodium EDTA, benzophenone-4, sodium benzoate, Citrus nobilis (mandarin orange) oil, Camellia sinensis leaf extract, Zingiber officinale (ginger) root oil, blue 1, yellow 5

ADVERSE REACTION

*This product is not manufactured or distributed by Colgate-Palmolive Company, distributor of Softsoap Antibacterial Liquid Hand Soap Fresh Citrus

DISTRIBUTED BY

MEIJER DISTRIBUTION, INC.

GRAND RAPIDS, MI 49544

www.meijer.com

principal display panel

NDC 79481-9633-1

meijer ®

ANTIBACTERIAL

hand soap

FRESH CITRUS

SCENT

HELPS KILL HARMFUL GERMS

Compare to Softsoap ®Hand Soap*

11.25 FL OZ (332 mL)